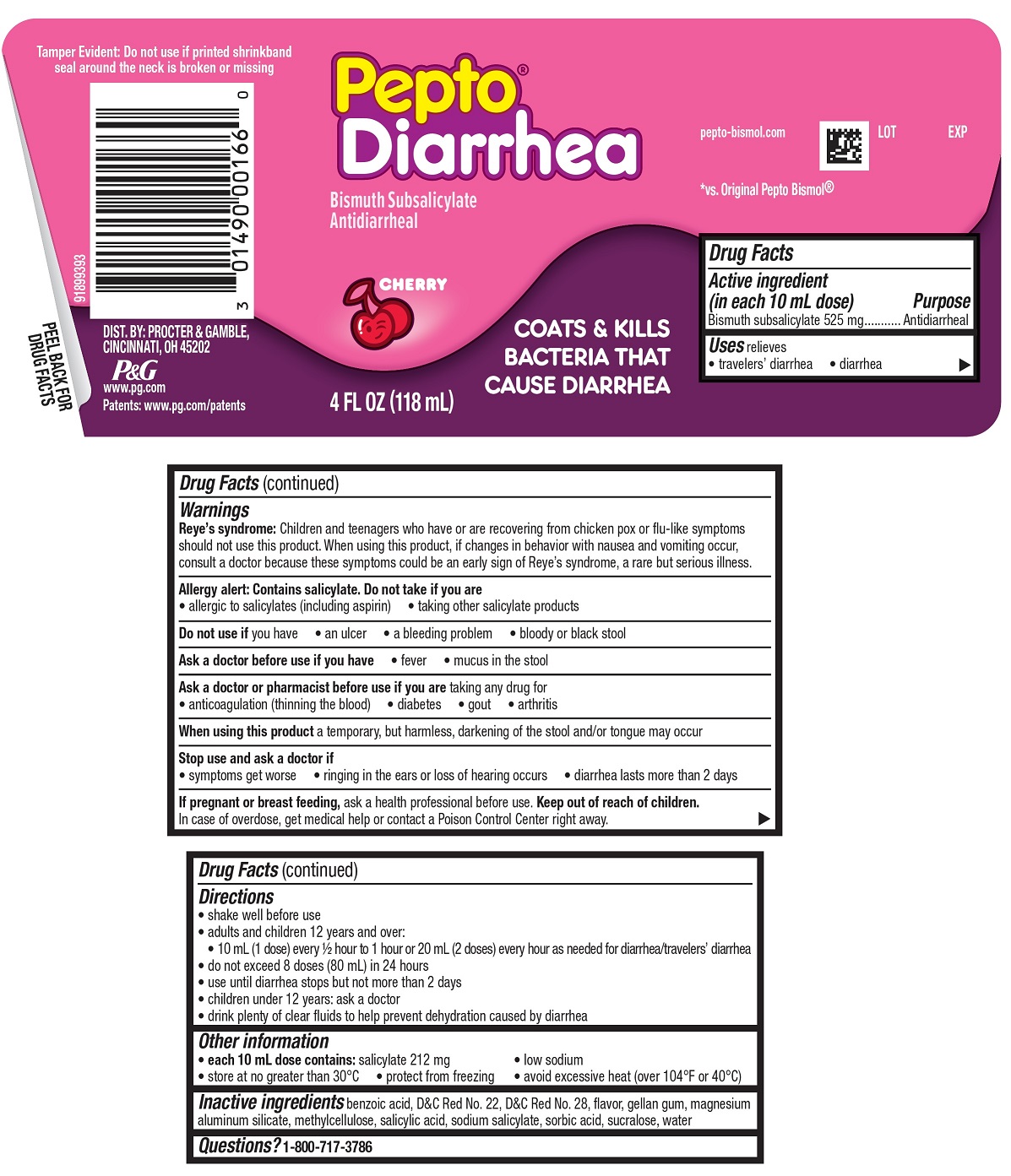 DRUG LABEL: Pepto
NDC: 37000-538 | Form: SUSPENSION
Manufacturer: The Procter & Gamble Manufacturing Company
Category: otc | Type: HUMAN OTC DRUG LABEL
Date: 20231128

ACTIVE INGREDIENTS: BISMUTH SUBSALICYLATE 525 mg/30 mL
INACTIVE INGREDIENTS: BENZOIC ACID; MAGNESIUM ALUMINUM SILICATE; D&C RED NO. 22; D&C RED NO. 28; SUCRALOSE; SALICYLIC ACID; SODIUM SALICYLATE; SORBIC ACID; WATER; GELLAN GUM (HIGH ACYL); METHYLCELLULOSE, UNSPECIFIED

Pepto® Diarrhea

Drug Facts

Active ingredient (in each 10 mL dose)

Bismuth subsalicylate 525 mg

Purpose

Antidiarrheal

Uses

relieves

- travelers' diarrhea
- diarrhea

Warnings

Reye's syndrome:

Children and teenagers who have or are recovering from chicken pox or flu-like symptoms should not use this product. When using this product, if changes in behavior with nausea and vomiting occur, consult a doctor because these symptoms could be an early sign of Reye's syndrome, a rare but serious illness.

Allergy alert:

Contains salicylate. Do not take if you are

- allergic to salicylates (including aspirin)
- taking other salicylate products

Do not use if

you have

- an ulcer
- a bleeding problem
- bloody or black stool

Ask a doctor before use if you have

- fever
- mucus in the stool

Ask a doctor or pharmacist before use if you are

taking any drug for

- anticoagulation (thinning the blood)
- diabetes
- gout
- arthritis

When using this product

a temporary, but harmless, darkening of the stool and/or tongue may occur

Stop use and ask a doctor if

- symptoms get worse
- ringing in the ears or loss of hearing occurs
- diarrhea lasts more than 2 days

If pregnant or breast-feeding,

ask a health professional before use.

Keep out of reach of children.

OVERDOSAGE

In case of overdose, get medical help or contact a Poison Control Center right away.

Directions

- shake well before use
- adults and children 12 years and over:
- 10 mL (1 dose) every ½ hour to 1 hour or 20 mL (2 doses) every hour as needed for diarrhea/travelers’ diarrhea
- do not exceed 8 doses (80 mL) in 24 hours
- use until diarrhea stops but not more than 2 days
- children under 12 years: ask a doctor
- drink plenty of clear fluids to help prevent dehydration caused by diarrhea

Other information

- each 10 mL dose contains:salicylate 212 mg
  - low sodium
  - store at no greater than 30°C
  - protect from freezing
  - avoid excessive heat (over 104°F or 40°C)

Inactive ingredients

benzoic acid, D&C Red No. 22, D&C Red No. 28, flavor, gellan gum, magnesium aluminum silicate, methylcellulose, salicylic acid, sodium salicylate, sorbic acid, sucralose, water

Questions?

1-800-717-3786

Tamper Evident: Do not use if printed shrinkband
seal around the neck is broken or missing

DIST. BY PROCTER & GAMBLE,
CINCINNATI OH 45202

PRINCIPAL DISPLAY PANEL - 118 mL Bottle Label

*vs. Original Pepto Bismol®

Pepto®

Diarrhea

Bismuth Subsalicylate

Antidiarrheal

CHERRY

COATS & KILLS BACTERIA THAT CAUSE DIARRHEA

4 FL OZ

(118 mL)